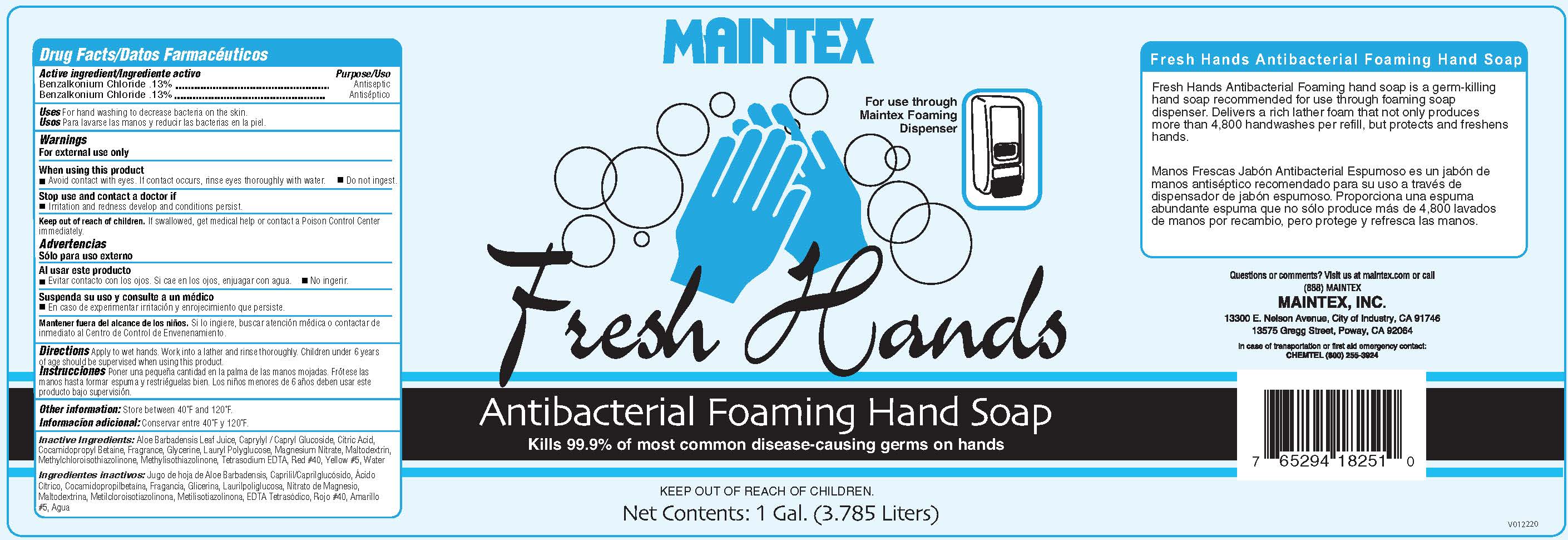 DRUG LABEL: Fresh Hands
NDC: 77617-009 | Form: LIQUID
Manufacturer: Maintex
Category: otc | Type: HUMAN OTC DRUG LABEL
Date: 20251222

ACTIVE INGREDIENTS: BENZALKONIUM CHLORIDE 13 kg/100 kg
INACTIVE INGREDIENTS: ALOE VERA LEAF; CAPRYLYL/CAPRYL OLIGOGLUCOSIDE; ANHYDROUS CITRIC ACID; COCAMIDOPROPYL BETAINE; GLYCERIN; LAURYL GLUCOSIDE; MAGNESIUM NITRATE; MALTODEXTRIN; METHYLCHLOROISOTHIAZOLINONE; METHYLISOTHIAZOLINONE; FD&C RED NO. 40; EDETATE SODIUM; WATER; FD&C YELLOW NO. 5

Fresh Hands

ACTIVE INGREDIENT

Benzalkonium Chloride..............0.13%

Purpose

Antiseptic

Uses

For hand washing to decrease bacteria on the skin.

Warnings

For external use only.

When Using this Product

- Avoid contact with the eyes.

- If contact occurs, rinse eyes thorougly with water. Do not ingest.

- Stop use and contact a doctor if irritation or redness develop

and conditions persist.

Keep out of reach of children. If swallowed, get medical help

or contact a Poison Control Center immediately.

Directions

-Apply to wet hands, work into a lather and rinse thoroughly.

-Children under 6 years of age should be supervised when using this product.

Inactive Ingredients

Water, Cocamidopropyl Betaine, Caprylyl Glucoside, Glycerine, Tetrasodium EDTA, Benzisothiazol, Methylisothiozol, Fragrance, Citric Acid, Aloe Vera, Yellow #5, Red #40.